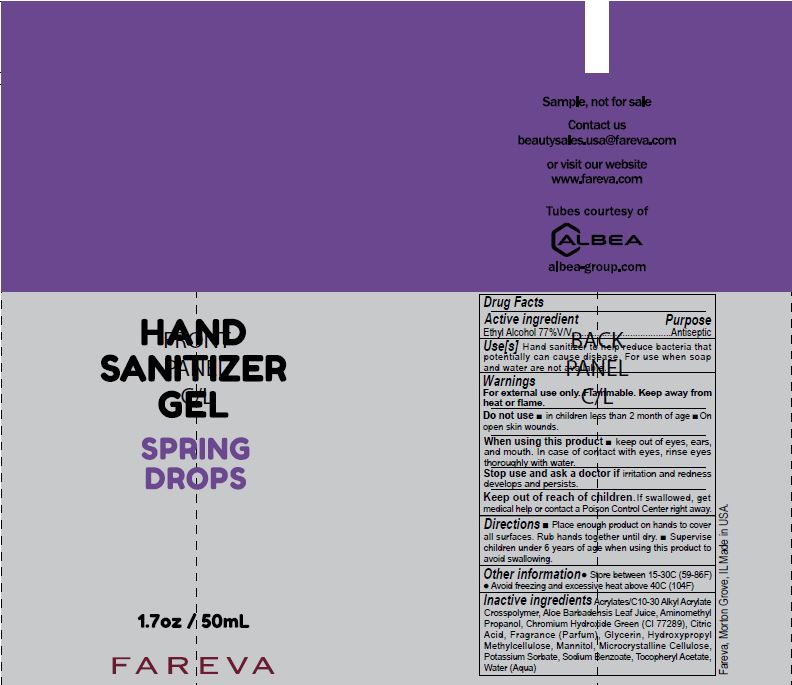 DRUG LABEL: Hand Sanitizer
NDC: 72686-189 | Form: GEL
Manufacturer: Fareva Morton Grove, Inc.
Category: otc | Type: HUMAN OTC DRUG LABEL
Date: 20210222

ACTIVE INGREDIENTS: ALCOHOL 77 mL/100 mL
INACTIVE INGREDIENTS: AMINOMETHYLPROPANOL; MICROCRYSTALLINE CELLULOSE; ALOE VERA LEAF; GLYCERIN; FRAGRANCE FLORAL ORC0902236; WATER; CHROMIUM HYDROXIDE GREEN; .ALPHA.-TOCOPHEROL ACETATE; MANNITOL; CITRIC ACID MONOHYDRATE; SODIUM BENZOATE; CARBOMER INTERPOLYMER TYPE A (55000 CPS); HYPROMELLOSES; POTASSIUM SORBATE

HAND SANITIZER GEL SPRING DROPS

This is a hand sanitizer manufactured according to the Temporary Policy for Preparation of Certain Alcohol-Based Hand Sanitizer Products During the Public Health Emergency (CoViD-19); Guidance for Industry.

1. Alcohol (ethanol) (USP or Food Chemical Codex (FCC) grade) (77%, volume/volume (v/v)) in an aqueous solution denatured according to Alcohol and Tobacco Tax and Trade Bureau regulations in 27 CFR part 20.
2. WATER (AQUA)
  c. GLYCERIN
  d. FRAGRANCE (PARFUM)
  e. ACRYLATES/C10-30 ALKYL ACRYLATE CROSSPOLYMER
  f. MANNITOL
  g. ALOE BARBADENSIS LEAF JUICE
  h. AMINOMETHYL PROPANOL
  i. MICROCRYSTALLINE CELLULOSE
  j. TOCOPHERYL ACETATE
  k. CHROMIUM HYDROXIDE GREEN (CI 77289)
  l. HYDROXYPROPYL METHYLCELLULOSE
  m. CITRIC ACID
  n. SODIUM BENZOATE
  o. POTASSIUM SORBATE

Active Ingredient(s)

Alcohol 77% v/v. Purpose: Antiseptic

Purpose

Antiseptic

Use

Hand Sanitizer to help reduce bacteria that potentially can cause disease. For use when soap and water are not available.

Warnings

For external use only. Flammable. Keep away from heat or flame

Do not use

- in children less than 2 months of age
- on open skin wounds

When using this product keep out of eyes, ears, and mouth. In case of contact with eyes, rinse eyes thoroughly with water.
Stop use and ask a doctor if irritation and redness develops and persists.

Keep out of reach of children. If swallowed, get medical help or contact a Poison Control Center right away.

Stop use and ask a doctor if irritation and redness develops and persists.

Keep out of reach of children. If swallowed, get medical help or contact a Poison Control Center right away.

Directions

- Place enough product on hands to cover all surfaces. Rub hands together until dry.
- Supervise children under 6 years of age when using this product to avoid swallowing.

Other information

- Store between 15-30C (59-86F)
- Avoid freezing and excessive heat above 40C (104F)

Inactive ingredients

ACRYLATES/C10-30 ALKYL ACRYLATE CROSSPOLYMER, ALOE BARBADENSIS LEAF JUICE, AMINOMETHYL PROPANOL, CHROMIUM HYDROXIDE GREEN (CI 77289), CITRIC ACID, FRAGRANCE (PARFUM), GLYCERIN, HYDROXYPROPYL METHYLCELLULOSE, MANNITOL, MICROCRYSTALLINE CELLULOSE, POTASSIUM SORBATE, SODIUM BENZOATE, TOCOPHERYL ACETATE, WATER (AQUA).

Package Label - Principal Display Panel

50 mL NDC: 72686-189-05